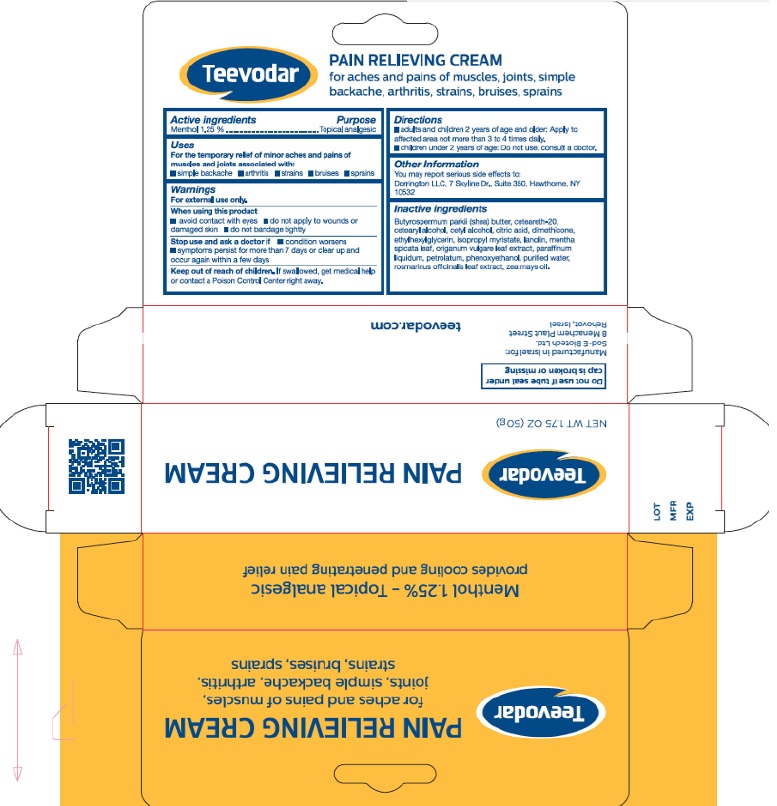 DRUG LABEL: Teevodar Pain Relieving
NDC: 84483-0001 | Form: CREAM
Manufacturer: Sod-e Biotech Ltd
Category: otc | Type: HUMAN OTC DRUG LABEL
Date: 20251217

ACTIVE INGREDIENTS: MENTHOL 12.5 mg/1 g
INACTIVE INGREDIENTS: CETOSTEARYL ALCOHOL; PHENOXYETHANOL; SPEARMINT; ISOPROPYL MYRISTATE; CETYL ALCOHOL; ANHYDROUS CITRIC ACID; OREGANO; PETROLATUM; SHEA BUTTER; POLYOXYL 20 CETOSTEARYL ETHER; LANOLIN; MINERAL OIL; WATER; ROSEMARY; DIMETHICONE; ETHYLHEXYLGLYCERIN; CORN OIL

Active ingredients

Menthol 1.25%

Purpose

Topical analgesic

Uses

For the temporary relief of minor aches and pains of muscles and joints associated with:

- Simple backache
- Arthritis
- Strains
- Bruises
- Sprains

Warnings

For external use only.

When using this product

- avoid contact with eyes
- do not apply to wounds or damaged skin
- do not bandage tightly

Stop use and ask a doctor if

- condition worsens
- symptoms persist for more than 7 days or clear up and occur again within a few days

Keep out of reach of children.

If swallowed, get medical help or contact a Poison Control Center right away.

Directions

- adults and children 2 years of age and older: Apply to affected area not more than 3 to 4 times daily.
- children under 2 years of age: Do not use, consult a doctor.

Other information

You may report serious side effects to: Dorrington LLC, 7 Skyline Dr., Suite 350, Hawthorne, NY 10532

Inactive ingredients

butyrospermum parkii (shea) butter, ceteareth-20, cetearyl alcohol, cetyl alcohol, citric acid, dimethicone, ethylhexlglycerin, isopropyl myristate, lanolin, mentha spicata leaf, origanum vulgare leaf extract, paraffinum liquidum, petrolatum, phenoxyethanol, purified water, rosmarinus officinalis leaf extract, zea mays oil